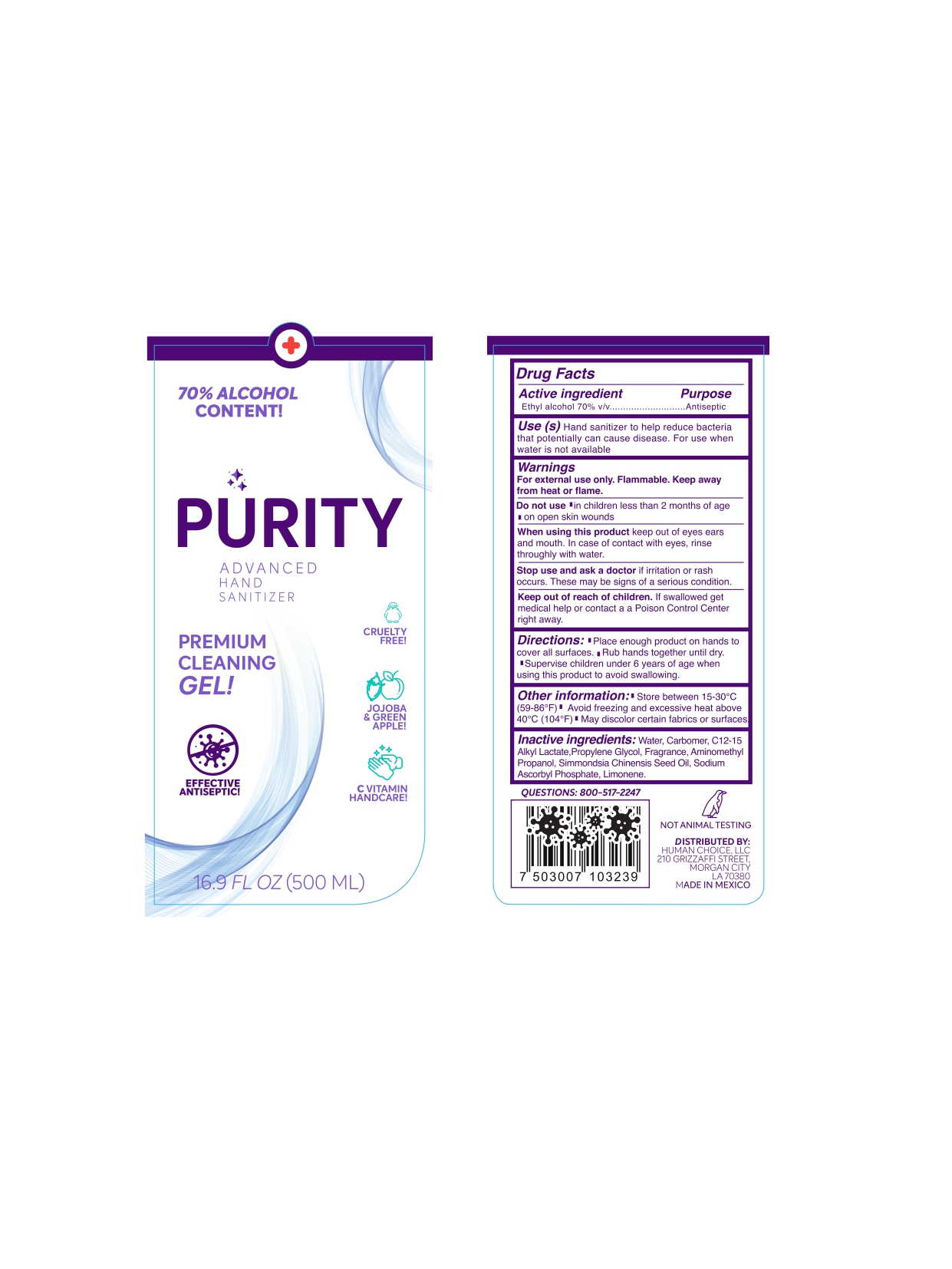 DRUG LABEL: Purity Hand Sanitizer
NDC: 75165-008 | Form: GEL
Manufacturer: Soluciones Cosmeticas SA de CV
Category: otc | Type: HUMAN OTC DRUG LABEL
Date: 20200630

ACTIVE INGREDIENTS: ALCOHOL 70 mL/100 mL
INACTIVE INGREDIENTS: PROPYLENE GLYCOL 0.3 mL/100 mL; AMINOMETHYLPROPANOL 0.1 mL/100 mL; CARBOMER HOMOPOLYMER, UNSPECIFIED TYPE 0.5 mL/100 mL; C12-15 ALKYL LACTATE 0.5 mL/100 mL; WATER 28.344 mL/100 mL; FRAGRANCE LAVENDER & CHIA F-153480 0.2 mL/100 mL; LIMONENE, (+)- 0.001 mL/100 mL; JOJOBA OIL 0.03 mL/100 mL; SODIUM ASCORBYL PHOSPHATE 0.025 mL/100 mL

Purity Hand Sanitizer
70%Alcohol + Jojoba + Vit C

Active Ingredient(s)

Alcohol 70% v/v. Purpose: Antiseptic

Purpose

Antiseptic, Hand Sanitizer

Use

Hand Sanitizer to help reduce bacteria that potentially can cause disease. For use when soap and water are not available.

Warnings

For external use only. Flammable. Keep away from heat or flame

Do not use

- in children less than 2 months of age
- on open skin wounds

When using this product keep out of eyes, ears, and mouth. In case of contact with eyes, rinse eyes thoroughly with water.
Stop use and ask a doctor if irritation or rash occurs. These may be signs of a serious condition.
Keep out of reach of children. If swallowed, get medical help or contact a Poison Control Center right away.

Stop use and ask a doctor if irritation or rash occurs. These may be signs of a serious condition.

Keep out of reach of children. If swallowed, get medical help or contact a Poison Control Center right away.

Directions

- Place enough product on hands to cover all surfaces. Rub hands together until dry.
- Supervise children under 6 years of age when using this product to avoid swallowing.

Other information

- Store between 15-30C (59-86F)
- Avoid freezing and excessive heat above 40C (104F)

Inactive ingredients

Water, Carbomer, C12-C15 Alkyl Lactate, Propylene Glycol, Fragrance, Aminomethyl Propanol, Simmondsia Chinensis Seed Oil, Sodium Ascorbyl Phosphate, Limonene.

Package Label - Principal Display Panel

500 mL NDC: 75165-008-01